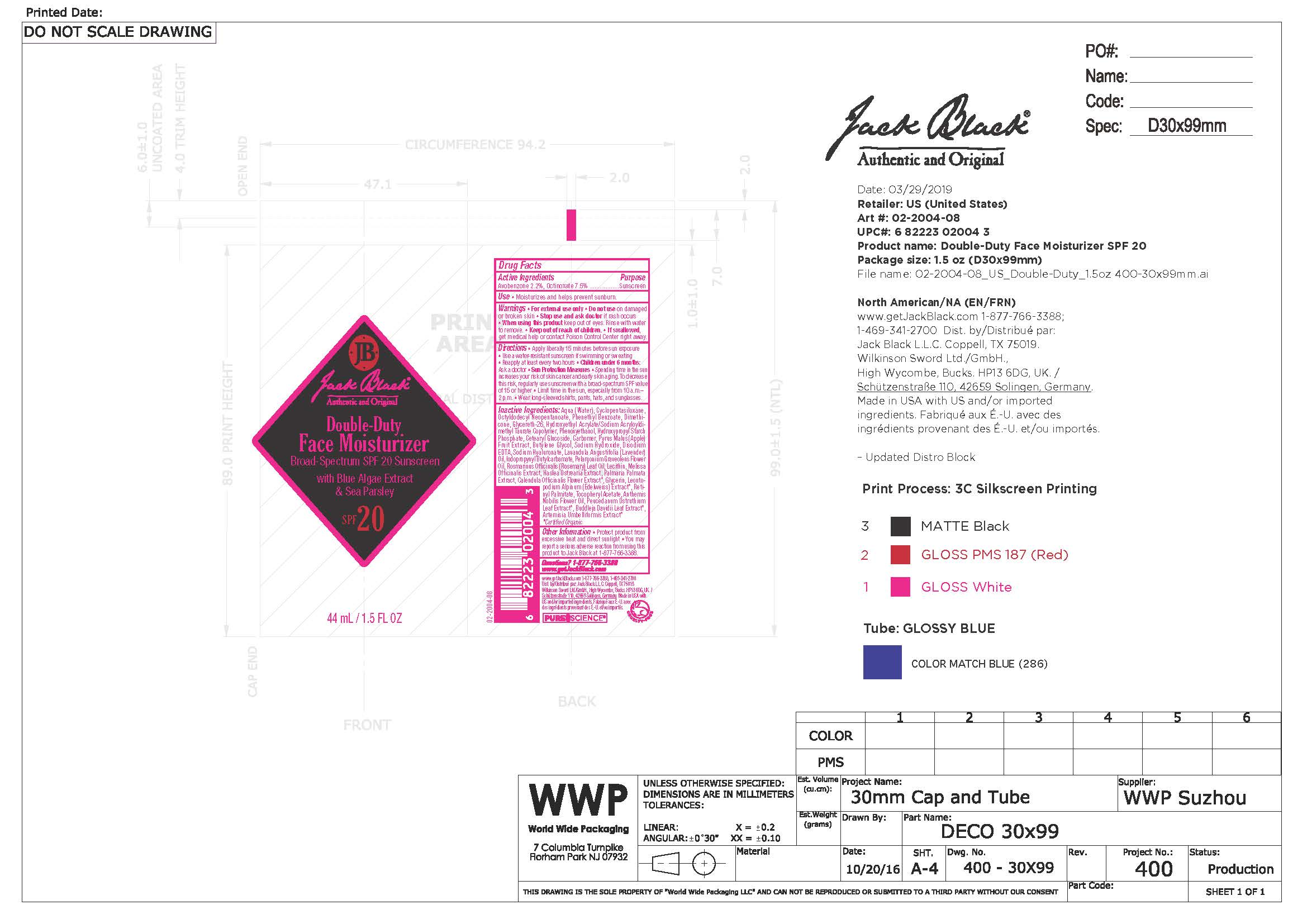 DRUG LABEL: Double-Duty Face Moisturizer
NDC: 66738-020 | Form: LOTION
Manufacturer: Jack Black, LLC
Category: otc | Type: HUMAN OTC DRUG LABEL
Date: 20231107

ACTIVE INGREDIENTS: AVOBENZONE 2.2 g/1000 g; OCTINOXATE 7.5 g/1000 g
INACTIVE INGREDIENTS: WATER; CYCLOMETHICONE; OCTYLDODECYL NEOPENTANOATE; PHENETHYL BENZOATE; HASLEA OSTREARIA; HYALURONATE SODIUM; LECITHIN, SOYBEAN; GLYCERIN; LAVENDER OIL; ROSEMARY OIL; MELISSA OFFICINALIS LEAF OIL; PEUCEDANUM OSTRUTHIUM LEAF; BUDDLEJA DAVIDII LEAF; PELARGONIUM GRAVEOLENS FLOWER OIL; DIMETHICONE; GLYCERETH-26; HYDROXYETHYL ACRYLATE/SODIUM ACRYLOYLDIMETHYL TAURATE COPOLYMER (100000 MPA.S AT 1.5%); PHENOXYETHANOL; CETEARYL GLUCOSIDE; CARBOMER 934; BUTYLENE GLYCOL; SODIUM HYDROXIDE; EDETATE DISODIUM; IODOPROPYNYL BUTYLCARBAMATE; DULSE; .ALPHA.-TOCOPHEROL ACETATE; VITAMIN A PALMITATE; CALENDULA OFFICINALIS FLOWER; LEONTOPODIUM NIVALE SUBSP. ALPINUM FLOWER; APPLE FRUIT OIL; ARTEMISIA UMBELLIFORMIS FLOWER; CHAMAEMELUM NOBILE FLOWER OIL; CARBOMER HOMOPOLYMER TYPE A (ALLYL PENTAERYTHRITOL CROSSLINKED)

Jack Black Double-Duty Face Moisturizer

Active Ingredients

Avobenzone 2.2% Sunscreen

Octinoxate 7.5% Sunscreen

Inactive Ingredients

Purified Water, Cyclopentasiloxane, Octyldodecyl Neopentanoate, Phenylethyl Benzoate, Dimethicone, Glycereth-26, Hydroxyethyl Acrylate / Sodium Acryloyl Dimethyl Taurate Copolymer, Phenoxyethanol, Hydroxypropyl Starch Phosphate, Cetearyl Glucoside, Carbomer, Pyrus Malus (Apple) Fruit Extract, Butylene Glycol, Sodium Hydroxide, Disodium EDTA, Sodium Hyaluronate, Lavendula Angustifolia (Lavender) Oil, Iodopropynyl Butylcarbamate, Pelargonium Graveolens (Geranium) Flower Oil, Rosmarinus Officinalis (Rosemary) Leaf Oil, Lecithin, Melissa Officinalis (Balm Mint) Extract, Haslea Ostreaia (Blue Algae) Extract, Palmaria Palmata (Sea Parsley) Extract, Calendula Officinalis (Calendula) Flower Extract, Glycerin, Leontopodium Alöinum (Edelweiss) Extract, Artemisia Umbelliformis Extract, Buddleja Davidii Leaf Extract, Peucedanum Ostruthium Leaf Extract, Tocopheryl Acetate, Retinyl Palmitate, Anthemis Nobilis (Roman Chamomile) Flower Oil

Use

Helps prevent sunburn

Use

Helps prevent sunburn

Warnings

- For external use only
- Do not use on damaged or broken skin
- Stop use and ask doctor if rash occurs
- When using this product keep out of eyes. Rinse with water to remove
- Keep out of reach of children
- If swallowed, get medical help or contact Poison Control Center right away

Directions

- Apply liberally 15 minutes before sun exposure
- Use a water resisitant sunscreen if swimming or sweating
- Reapply at least every two hours
- Children under 6 months: ask a doctor.
- Sun Protection Measures:
- Spending time in the sun increases your risk of skin cancer and early skin aging. To decrease this risk, use sunscreen with a broad spectrum SPF15 or higher
- Limit time in the sun, especxially from 10 a.m. - 2 p.m.
- Wear long sleeve shirts, pants, hats and sunglasses.

KEEP OUT OF REACH OF CHILDREN

Other Information

Protect product from excessive heat and driect sunlight. You may report a serious adverse reaction from using this product to Jack Black at 1-877-766-3388.

Questions?

1-877-766-3388

www.getjackblack.com